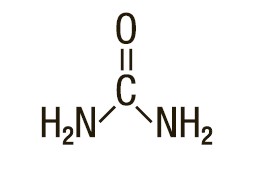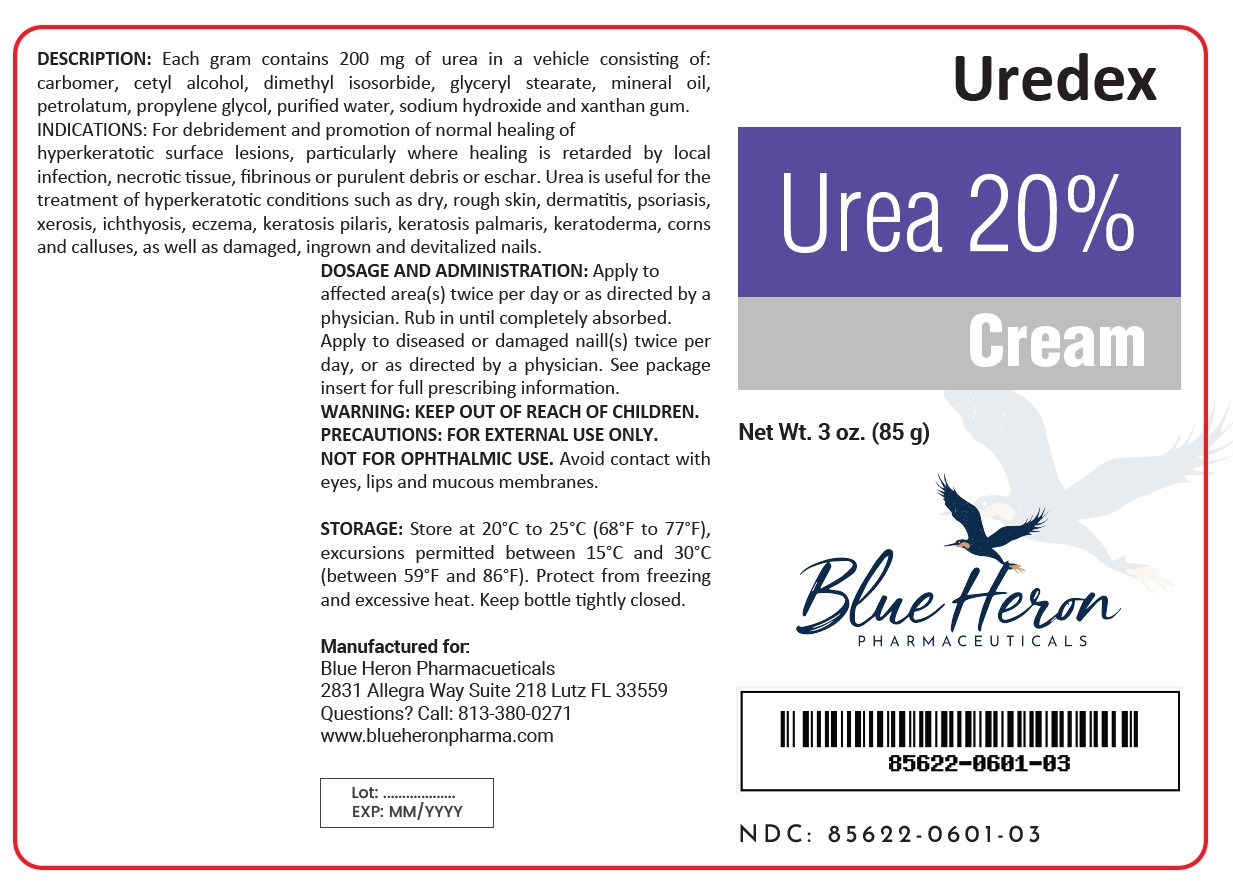 DRUG LABEL: UREDEX
NDC: 85622-601 | Form: CREAM
Manufacturer: Blue Heron Pharmaceuticals, LLC
Category: prescription | Type: HUMAN PRESCRIPTION DRUG LABEL
Date: 20260116

ACTIVE INGREDIENTS: UREA 200 mg/1 g
INACTIVE INGREDIENTS: CARBOMER INTERPOLYMER TYPE A (55000 CPS); CETYL ALCOHOL; GLYCERYL MONOSTEARATE; PROPYLENE GLYCOL; PETROLATUM; SODIUM HYDROXIDE; MINERAL OIL; XANTHAN GUM; DIMETHYL ISOSORBIDE; WATER

Uredex

Uredex Cream

Rx Only

FOR EXTERNAL USE ONLY. NOT FOR OPHTHALMIC USE.

DESCRIPTION:

Each gram contains 200 mg of urea in a vehicle consisting of: carbomer, cetyl alcohol, dimethyl isosorbide, glyceryl stearate, mineral oil, petrolatum, propylene glycol, purified water, sodium hydroxide and xanthan gum.

Urea is a diamide of carbonic acid with the following chemical structure:

CLINICAL PHARMACOLOGY:

Urea gently dissolves the intercellular matrix which results in loosening the horny layer of skin and shedding scaly skin at regular intervals, thereby softening hyperkeratotic areas of the skin.

Pharmacokinetics: The mechanism of action of topically applied urea is not yet known.

INDICATIONS:

For debridement and promotion of normal healing of hyperkeratotic surface lesions, particularly where healing is retarded by local infection, necrotic tissue, fibrinous or purulent debris or eschar. Urea is useful for the treatment of hyperkeratotic conditions such as dry, rough skin, dermatitis, psoriasis, xerosis, ichthyosis, eczema, keratosis pilaris, keratosis palmaris, keratoderma, corns and calluses, as well as damaged, ingrown and devitalized nails.

CONTRAINDICATIONS:

This product is contraindicated in persons with known or suspected hypersensitivity to any of the ingredients of the product.

WARNING:

KEEP OUT OF REACH OF CHILDREN.

PRECAUTIONS:

FOR EXTERNAL USE ONLY. NOT FOR OPHTHALMIC USE.

General: This product is to be used as directed by a physician and should not be used to treat any condition other than that for which it was prescribed. If redness or irritation occurs, discontinue use and consult a physician.

Information for Patients: Patients should discontinue the use of this product if the condition becomes worse or if a rash develops in the area being treated or elsewhere. Avoid contact with eyes, lips and mucousmembranes.

Carcinogenesis, Mutagenesis and Impairment of Fertility: Long-term animal studies for carcinogenic potential have not been performed on this product to date. Studies on reproduction and fertility also have not been performed.

Pregnancy: Category C. Animal reproduction studies have not been conducted with this product. It is also not known whether this product can affect reproduction capacity or cause fetal harm when administered to a pregnant woman. This product should be used by a pregnant woman only if clearly needed or when potential benefits outweigh potential hazards to the fetus.

Nursing Mothers: It is not known whether this drug is excreted in human milk. Because many drugs are excreted in human milk, caution should be exercised when this product is administered to a nursing woman.

ADVERSE REACTIONS:

Transient stinging, burning, itching or irritation may occur and normally disappear upon discontinuing the use of this product.

DOSAGE AND ADMINISTRATION:

Apply to affected area(s) twice per day or as directed by a physician. Rub in until completely absorbed.

Apply to diseased or damaged nail(s) twice per day, or as directed by a physician.

STORAGE:

Store at 20°C to 25°C (68°F to 77°F), excursions permitted between 15°C to 30°C (between 59°F to 86°F). Brief exposure to temperatures up to 40°C (104°F) may be tolerated provided the mean kinetic temperature does not exceed 25°C (77°F);
however, such exposure should be minimized.

NOTICE: Protect from freezing and excessive heat. Keep bottle tightly closed.

HOW SUPPLIED:

3 oz. (85 g) bottles, NDC 85622-0601-03

To report a serious adverse event or obtain product information, call (813) 380-0271.

Manufactured for:

Blue Heron Pharmacueticals, LLC

2831 Allegra Way, Suite 218, Lutz, FL 33559

Questions? Call: (813) 380-0271